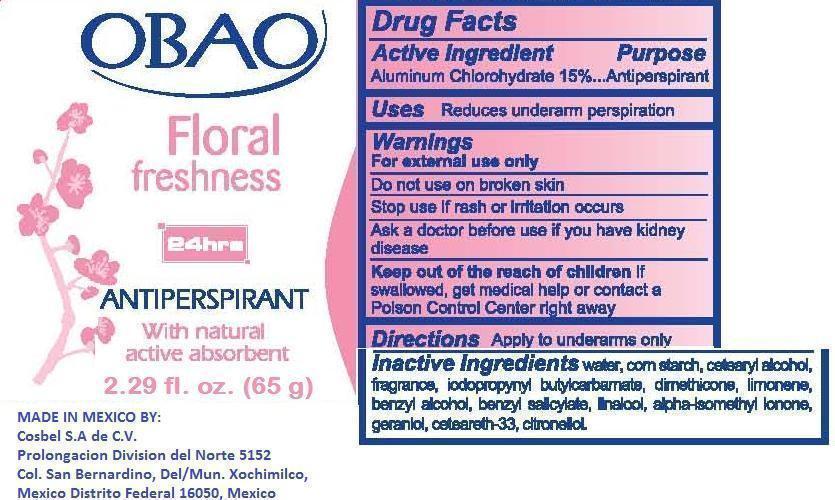 DRUG LABEL: Obao
NDC: 51769-123 | Form: STICK
Manufacturer: ALL NATURAL DYNAMICS
Category: otc | Type: HUMAN OTC DRUG LABEL
Date: 20130729

ACTIVE INGREDIENTS: ALUMINUM CHLOROHYDRATE 15 g/100 g
INACTIVE INGREDIENTS: WATER; STARCH, CORN; CETOSTEARYL ALCOHOL; IODOPROPYNYL BUTYLCARBAMATE; DIMETHICONE; LIMONENE, (+)-; BENZYL ALCOHOL; BENZYL SALICYLATE; LINALOOL, DL-; GERANIOL; .BETA.-CITRONELLOL, (+/-)-

Obao Floral Freshness

Warnings:

For External Use Only. Do Not Apply On Irritated Or Injured Skin. Discontinue Use If You Experience Some Irritation, Redness Or Discomfort.

Active Ingredient:

Aluminum Chlorohydrate 15%

Purpose

Anti Perspirant

Keep Out Of The Reach Of Children

USE:

reduces underarm persperation

Directions:

Apply under arm only.

SHAKE WELL BEFORE USE.

Inactive Ingredients:

Water , Cornstarch , Cetearyl Alcohol , Fragrance , Iodopropynyl Butylcarbamate , Dimethicone , Limonene , Benzyl Alcohol , Benzyl Salicylate , Linalool , Alpha-Isomethyl Ionone , Geraniol , Ceteareth-33 , Citronellol